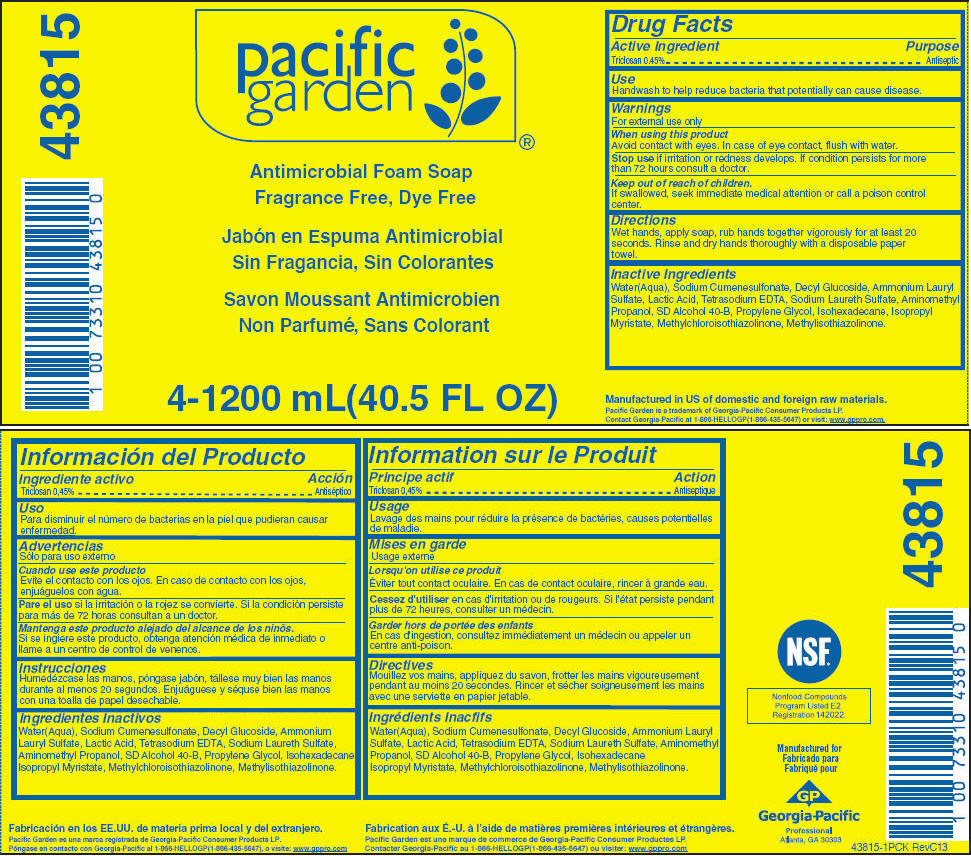 DRUG LABEL: Pacific Garden
NDC: 54622-687 | Form: SOAP
Manufacturer: Georgia-Pacific Consumer Products LP
Category: otc | Type: HUMAN OTC DRUG LABEL
Date: 20181231

ACTIVE INGREDIENTS: TRICLOSAN 4.5 mg/1 mL
INACTIVE INGREDIENTS: PROPYLENE GLYCOL; WATER; ALCOHOL; AMMONIUM LAURYL SULFATE; SODIUM CUMENESULFONATE; DECYL GLUCOSIDE; LACTIC ACID; EDETATE SODIUM; AMINOMETHYLPROPANOL; ISOPROPYL MYRISTATE; ISOHEXADECANE; METHYLCHLOROISOTHIAZOLINONE; METHYLISOTHIAZOLINONE; SODIUM LAURETH-3 SULFATE

Pacific Garden Antimicrobial Foam Soap, Fragrance Free, Dye Free

Drug Facts

Active Ingredient

Triclosan 0.45%

Purpose

Antiseptic

Use

Handwash to help reduce bacteria that potentially can cause disease.

Warnings

For external use only

When using this product

Avoid contact with eyes. In case of eye contact, flush with water.

Stop use if irritation or redness develops. If condition persists for more than 72 hours consult a doctor.

Keep out of reach of children.

If swallowed, seek immediate medical attention or call a poison control center.

Directions

Wet hands, apply soap, rub hands together vigorously for at least 20 seconds. Rinse and dry hands thoroughly with a disposable paper towel.

Inactive Ingredients

Water(Aqua), Sodium Cumenesulfonate, Decyl Glucoside, Ammonium Lauryl Sulfate, Lactic Acid, Tetrasodium EDTA, Sodium Laureth Sulfate, Aminomethyl Propanol, SD Alcohol 40-B, Propylene Glycol, Isohexadecane, Isopropyl Myristate, Methylchloroisothiazolinone, Methylisothiazolinone.

PRINCIPAL DISPLAY PANEL - 1200 mL Bag Label

pacific
garden

Antimicrobial Foam Soap
Fragrance Free, Dye Free

4-1200 mL(40.5 FL OZ)